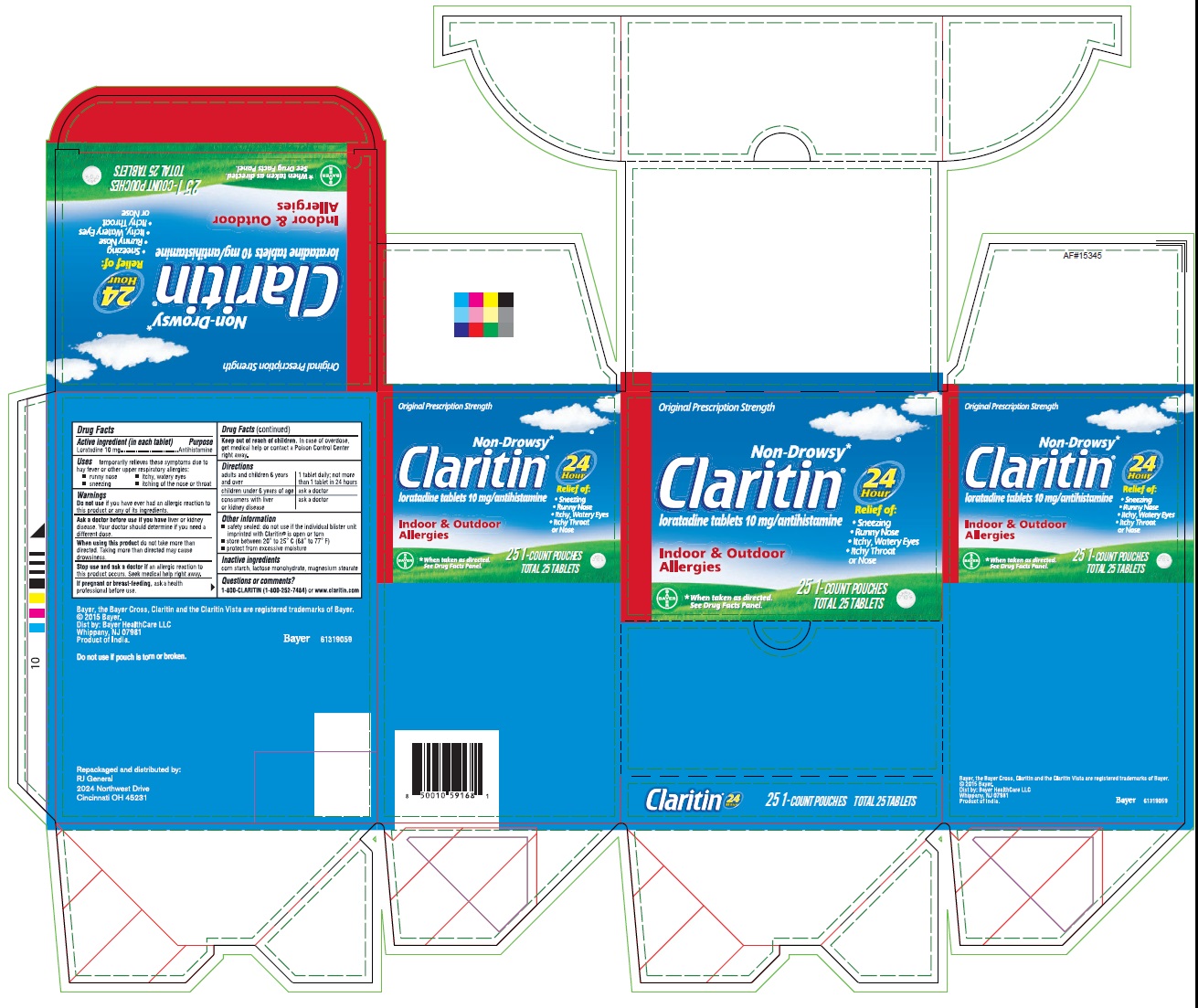 DRUG LABEL: Claritin
NDC: 70264-030 | Form: TABLET
Manufacturer: R J General Corporation
Category: otc | Type: HUMAN OTC DRUG LABEL
Date: 20251117

ACTIVE INGREDIENTS: LORATADINE 10 mg/1 1
INACTIVE INGREDIENTS: LACTOSE MONOHYDRATE; MAGNESIUM STEARATE; STARCH, CORN

Drug Facts

CLARITIN®

Active ingredients (in each tablet) | Purpose
Loratadine 10 mg | Antihistamine

USE

temporarily relieves these symptoms due to hay fever or other upper respiratory allergies:

- runny nose
- itchy, watery eyes
- sneezing
- itching of the nose or throat

WARNINGS

Do not use if you have ever had an allergic reaction to this product or any of its ingredients.

Ask a doctor before use if you have liver or kidney disease. your doctor should determine if you need a different dose.

When using this productdon not take more than directed. Taking more than directed may cause drowsiness.

Stop use and ask doctor ifan allergic reaction to this product occurs. Seek medical help right away.

If pregnant or breast-feeding,ask health professional before use.

Keep out of reach of children.in case of overdose, get medical help or contact a Poison Control Center right away.

Directions

adults and children 6 years and over | 1 tablet daily: not more than 1 tablet in 24 hours
children under 6 years of age | ask a doctor
consumer with liver or kidney disease | ask a doctor

Other information

- Safety sealed: do not use if the individual blister unit imprinted with Claritin® is open or torn
- Store between 20o to 25o C(68oto 77oF)
- Protect from excessive moisture

Inactive ingredients

Corn starch, lactose monohydrate, magnesium stearate

Questions and Comments?

1-800-CLARITIN(1-800-252-7484)or www.claritin.com

Dist. by: Bayer HealthCare LLC

Whippany, NJ 07981

Product of India

Do not use if pouch is torn or broken.

Repackaged and distributed by:

RJ General

2024 Northwest Drive

Cincinnati OH 45231

PRINCIPAL DISPLAY PANEL - 25 Tablet Pouch Carton

Non-Drowsy*

Claritin®

loratadine tablets 10 mg/ antihistamine

Indoor & Outdoor Allergies

Relief of:

- runny nose
- itchy, watery eyes
- sneezing
- itching of the throat or nose